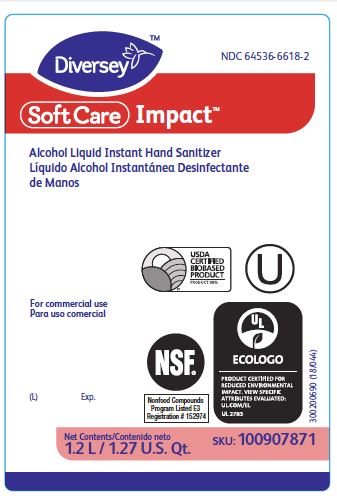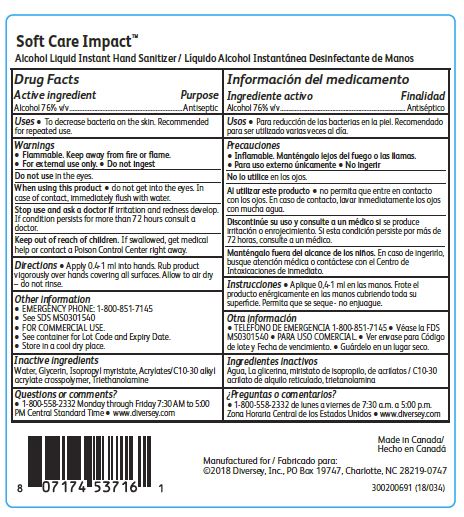 DRUG LABEL: Soft Care Impact Alcohol Instant Hand Sanitizer
NDC: 64536-6618 | Form: LIQUID
Manufacturer: Diversey, Inc.
Category: otc | Type: HUMAN OTC DRUG LABEL
Date: 20241216

ACTIVE INGREDIENTS: ALCOHOL 76 L/100 L
INACTIVE INGREDIENTS: WATER; GLYCERIN; ISOPROPYL MYRISTATE; CARBOMER INTERPOLYMER TYPE A (ALLYL SUCROSE CROSSLINKED); TROLAMINE

Drug Facts

Active ingredient

Alcohol 76% v/v

Purpose

Antiseptic

Uses

To decrease bacteria on the skin.

Recommended for repeated use.

Warnings

Flammable. Keep away from fire or flame.

For external use only.

Do not ingest.

Do not use in the eye.

When using this product do not get into the eyes.

In case of contact, immediately flush with water.

Stop use and ask a doctor if irritation and redness develop.

If condition persists for more than 72 hours consult a doctor.

Keep out of reach of children.

If swallowed, get medical help or contact a Poison control Center right away.

Directions

Apply 0.4-1 ml into hands.

Rub product vigorously over hands covering all surfaces.

Allow to air dry - do not rinse.

Other information

EMERGENCY PHONE: 1-800-851-7145

See SDS MS0301540

FOR COMMERCIAL USE.

See container for Lot Code and Expiry Date.

Store in a cool dry place.

Inactive ingredients

Water, Glycerin, Isopropyl myristate, Acrylates/C10-30 alkyl acrylate crosspolymer, Triethanolamine

Questions or comments?

1-800-558-2332 Monday through Friday 7:30 to 5:00 PM Central Standard Time

www.diversey.com

PACKAGE LABEL

NDC 64536-6618-2

Diversey

SofCare Impact

Alcohol Liquid Instant Hand Sanitizer

USDA

CERTIFIED

BIOBASED

PRODUCT

Product 96%

U

For commercial use

NSF

Nonfood Compounds

Program Listed E3

Registration #152974

UL

ECOLOGO

(L) Exp.

Net Contents

1.2 L/1.27 U.S. Qt.

SKU: 100907871